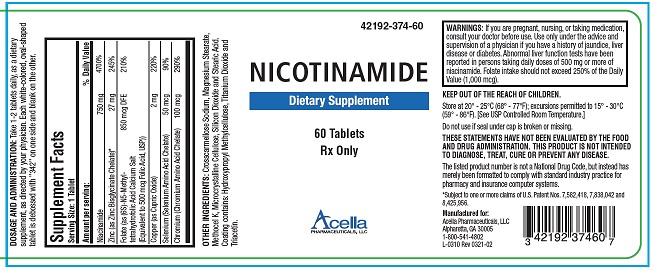 DRUG LABEL: Nicotinamide
NDC: 42192-374 | Form: TABLET
Manufacturer: Acella Pharmaceuticals, LLC 
Category: prescription | Type: HUMAN PRESCRIPTION DRUG LABEL
Date: 20250213

ACTIVE INGREDIENTS: NIACINAMIDE 750 mg/1 1; ZINC 27 mg/1 1; FOLIC ACID 850 ug/1 1; COPPER 2 mg/1 1; SELENIUM 50 ug/1 1; CHROMIUM 100 ug/1 1
INACTIVE INGREDIENTS: CROSCARMELLOSE SODIUM; MAGNESIUM STEARATE; HYPROMELLOSE 2208 (100 MPA.S); MICROCRYSTALLINE CELLULOSE; SILICON DIOXIDE; STEARIC ACID; HYPROMELLOSE, UNSPECIFIED; TITANIUM DIOXIDE; TRIACETIN

NICOTINAMIDE

STATEMENT OF IDENTITY

RX Only

Dietary Supplement

DESCRIPTION: Nicotinamide Tablets is a prescription dietary supplement for oral administration, specifically formulated for the dietary management of patients with unique nutritional needs who require increased levels of one or more of the ingredients in this product. Each white-colored, oval-shaped tablet is debossed with “342” on one side and blank on the other.

Supplement Facts
Serving Size: 1 Tablet
Amount per serving: |  | % Daily Value
Nicotinamide | 750 mg | 4700%
Zinc (as Zinc Bisglycinate Chelate)* | 27 mg | 245%
Folate (as (6S)-N5-Methyl- tetrahydrofolic Acid Calcium Salt | 850 mcg DFE | 210%
(Equivalent to 500 mcg Folic Acid, USP)) | 850 mcg DFE | 210%
Copper (as Cupric Oxide) | 2 mg | 220%
Selenium (Selenium Amino Acid Chelate) | 50 mcg | 90%
Chromium (Chromium Amino Acid Chelate) | 100 mcg | 290%

OTHER INGREDIENTS: Crosscarmellose Sodium, Magnesium Stearate, Methocel K, Microcrystalline Cellulose, Silicon Dioxide and Stearic Acid. Coating contains: Hydroxypropyl Methylcellulose, Titanium Dioxide and Triacetin.

INDICATIONS: Nicotinamide Tablets is indicated for use as a dietary supplement for patients who are deficient in, or who are at risk for deficiency in one or more of the ingredients in this product.

CONTRAINDICATIONS: This product is contraindicated in patients with a known hypersensitivity to any of the ingredients.

PRECAUTIONS

PRECAUTIONS: Large doses of Nicotinamide Tablets should be administered with caution in patients with a history of jaundice, liver disease, or diabetes. Patients with chronic liver failure and/or renal failure should exercise extreme caution in taking prescribed supplements containing copper.

Folic acid alone is improper treatment of pernicious anemia and other megaloblastic anemias where vitamin B12 is deficient. Folic acid especially in doses above 1.0 mg daily may obscure pernicious anemia in that hematologic remission may occur while neurological manifestations remain progressive

WARNINGS

THESE STATEMENTS HAVE NOT BEEN EVALUATED BY THE FOOD AND DRUG ADMINISTRATION. THIS PRODUCT IS NOT INTENDED TO DIAGNOSE, TREAT, CURE, OR PREVENT ANY DISEASE.

KEEP THIS AND ALL MEDICATIONS OUT OF THE REACH OF CHILDREN.

WARNINGS: If you are pregnant, nursing, or taking medication, consult your doctor before use. Use only under the advice and supervision of a physician if you have a history of jaundice, liver disease or diabetes. Abnormal liver function tests have been reported in persons taking daily doses of 500 mg or more of niacinamide. Folate intake should not exceed 250% of the Daily Value (1,000 mcg).

PREGNANCY & NURSING MOTHERS:

Nicotinamide Tablets is not indicated for use as a prenatal/postnatal multivitamin for lactating and nonlactating mothers. Physicians and medical practitioners should administer Nicotinamide Tablets with caution to patients who are pregnant, lactating and/or taking medication.

ADVERSE REACTIONS: Allergic sensitization has been reported rarely following oral and parental administration of Folate.

DOSAGE AND ADMINISTRATION: Take 1-2 tablets daily, as a dietary supplement, as directed by your physician.

HOW SUPPLIED: Nicotinamide Tablets are white-colored, oval-shaped tablets debossed on one side with “342”, and are supplied in bottles of 60 tablets (42192-374-60). The listed product number is not a National Drug Code. Instead, Acella has assigned a product code formatted according to standard industry practice in order to comply with the formatting requirements of pharmacy and healthcare insurance computer systems.

STORAGE: Store at 20° - 25°C (68° - 77°F); excursions permitted to 15° - 30°C (59° - 86°F). [See USP Controlled Room Temperature.]

MANUFACTURED FOR:

Acella Pharmaceuticals, LLC Alpharetta, GA 30005

1-800-541-4802

L-0289 Rev 0321-01

*Subject to one or more claims of U.S. Patent Nos. 7,582,418, 7,838,042 and 8,425,956.